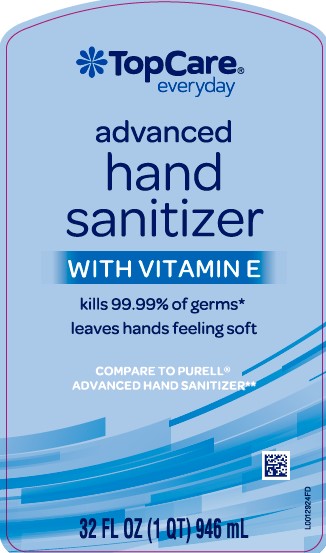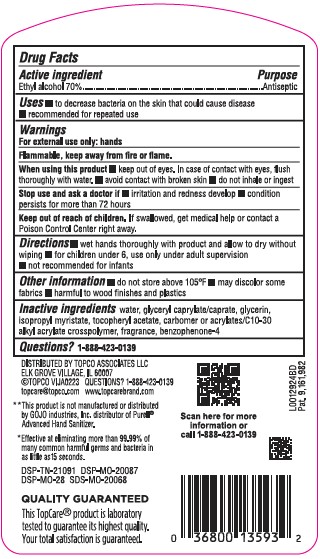 DRUG LABEL: Advanced
NDC: 36800-370 | Form: GEL
Manufacturer: Topco Associates LLC
Category: otc | Type: HUMAN OTC DRUG LABEL
Date: 20260213

ACTIVE INGREDIENTS: ALCOHOL 70 mL/100 mL
INACTIVE INGREDIENTS: WATER; GLYCERYL CAPRYLATE/CAPRATE; GLYCERIN; ISOPROPYL MYRISTATE; CARBOMER HOMOPOLYMER, UNSPECIFIED TYPE; CARBOMER COPOLYMER TYPE A (ALLYL PENTAERYTHRITOL CROSSLINKED); SULISOBENZONE; .ALPHA.-TOCOPHEROL ACETATE

Top Care 370.001/370AB-AE rev 1
Advanced Hand Sanitizer

Active ingredient

Ethyl alcohol 70%

Purpose

Antiseptic

Uses

- to decrease bacteria on the skin that could cause disease
- recommended for repeated use

Warnings

For external use only: hands

Flammable, keep away from fire or flame.

When using this product

- keep out of eyes. In case of contact with eyes, flush thoroughly with water.
- avoid contact with broken skin
- do not inhale or ingest

Stop use and ask a doctor if

■ irritation and redness develop
■ condition persists for more than 72 hours

Keep out of reach of children.

If swallowed, get medical help or contact a Poison Control Center right away.

Directions

- wet hands thoroughly with product and allow to dry without wiping
- for children under 6, use only under adult supervision
- not recommended for infants

Disclaimer

- do not store above 105⁰F
- may discolor some fabrics
- harmful to wood finishes and plastics

Inactive ingredients

water, glyceryl caprylate/caprate, glycerin, isopropyl myristate, tocopheryl acetate, carbomer or acrylates/C10-30 alkyl acrylate crosspolymer, fragrance, benzophenone-4

Questions?

1-888-423-0139

Adverse event

DISTRIBUTED BY TOPCO ASSOCIATES LLC

ELK GROVE VILLAGE, IL 60007

©TOPCO VIJA0223 QUESTIONS? 1-888-423-0139

topcare@topco.com WWW.TOPCAREBRAND.COM

**This product is not manufactured or distributed by GOJO Industries, Inc. distributor of Purell®Refreshing Gel Advanced Hand Sanitizer.

*Effective at eliminating more than 99.99% of many common harmful germs and bacteria in as little as 15 seconds.

DSP-TN-21091 DSP-MO-20087

DSP-MO-28 SDS-MO-20068

QUALITY GUARANTEED

This TopCare®product is laboratory tested to guarantee its highest quality.

Your total satisfaction is guaranteed.

Scan here for more information or call 1-888-423-0139

Pat. 9,161,982

Principal display panel

TopCare®

everyday

advanced

hand

sanitizer

WITH VITAMIN E

kills 99.9 of harmful germs*

leaves hands feeling soft

COMPARE TO PURELL®ADVANCED HAND SANITIZER**

32 FL OZ (1 QT) 946 mL